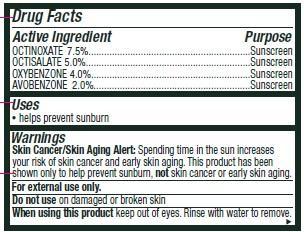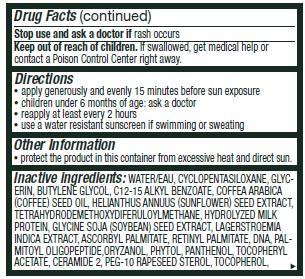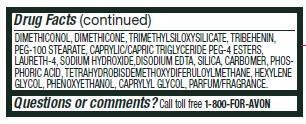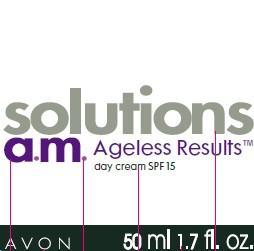 DRUG LABEL: Solutions
NDC: 10096-0178 | Form: CREAM
Manufacturer: Avon Products, Inc
Category: otc | Type: HUMAN OTC DRUG LABEL
Date: 20130123

ACTIVE INGREDIENTS: OCTINOXATE 75 mg/1 mL; OCTISALATE 50 mg/1 mL; OXYBENZONE 40 mg/1 mL; AVOBENZONE 20 mg/1 mL

Active Ingredient
OCTINOXATE 7.5%.........................................................
OCTISALATE 5.0%.........................................................
OXYBENZONE 4.0%.........................................................
AVOBENZONE 2.0%.......................................................

Purpose
...............Sunscreen
...............Sunscreen
.............Sunscreen
..........Sunscreen

Uses
• helps prevent sunburn

Warnings
Skin Cancer/Skin Aging Alert: Spending time in the sun increases your risk of skin cancer and early skin aging. This product has been shown only to help prevent sunburn, not skin cancer or early skin aging.

For external use only

Do not use on damaged or broken skin

When using this product keep out of eyes. Rinse with water to remove.

Stop use and ask a doctor if rash occurs

Keep out of reach of children. If swallowed, get medical help or contact a Poison Control Center right away.

Directions

• apply liberally 15 minutes before sun exposure
• children under 6 months of age: ask a doctor
• reapply at least every 2 hours
• use a water resistant sunscreen if swimming or sweating

Other information
• protect the product in this container from excessive heat and direct sun

INACTIVE INGREDIENT

Inactive ingredients: WATER/EAU, CYCLOPENTASILOXANE, GLYCERIN, BUTYLENE GLYCOL, C12-15 ALKYL BENZOATE, COFFEA ARABICA
(COFFEE) SEED OIL, HELIANTHUS ANNUUS (SUNFLOWER) SEED EXTRACT, TETRAHYDRODEMETHOXYDIFERULOYLMETHANE, HYDROLYZED MILK
PROTEIN, GLYCINE SOJA (SOYBEAN) SEED EXTRACT, LAGERSTROEMIA INDICA EXTRACT, ASCORBYL PALMITATE, RETINYL PALMITATE, DNA, PALMITOYL OLIGOPEPTIDE,ORYZANOL, PHYTOL, PANTHENOL, TOCOPHERYL ACETATE, CERAMIDE 2, PEG-10 RAPESEED STEROL, TOCOPHEROL, DIMETHICONOL, DIMETHICONE, TRIMETHYLSILOXYSILICATE, TRIBEHENIN, PEG-100 STEARATE, CAPRYLIC/CAPRIC TRIGLYCERIDE PEG-4 ESTERS, LAURETH-4, SODIUM HYDROXIDE,DISODIUM EDTA, SILICA, CARBOMER, PHOSPHORIC ACID, TETRAHYDROBISDEMETHOXYDIFERULOYLMETHANE, HEXYLENE GLYCOL, PHENOXYETHANOL, CAPRYLYL GLYCOL, PARFUM/FRAGRANCE.

Questions or Comments?
Call toll free 1-800-FOR-AVON